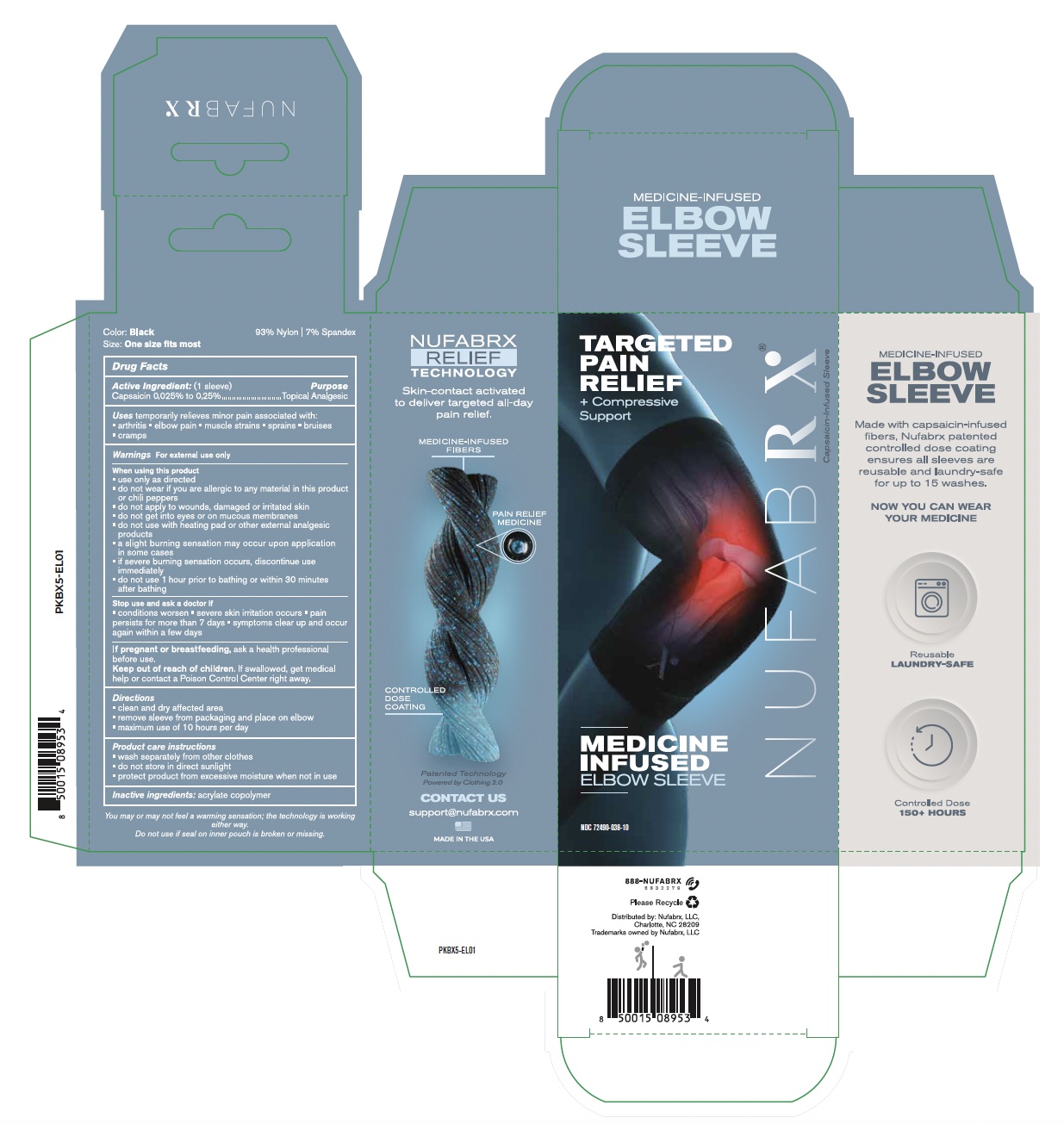 DRUG LABEL: Nufabrx Medicine Infused Elbow Sleeve
NDC: 72490-038 | Form: CLOTH
Manufacturer: Nufabrx LLC
Category: otc | Type: HUMAN OTC DRUG LABEL
Date: 20251015

ACTIVE INGREDIENTS: CAPSAICIN 0.25 g/100 g
INACTIVE INGREDIENTS: BUTYL ACRYLATE/METHYL METHACRYLATE/METHACRYLIC ACID COPOLYMER (18000 MW)

72490-038 Nufabrx Medicine Infused Elbow Sleeve

Active ingredient

Capsaicin 0.025% to 0.25%

Purpose

Topical Analgesic

Uses

Temporary relieves minor pain associated with:

- arthritis
- elbow pain
- muscle strains
- sprains
- bruises
- cramps

Warnings

For external use only.

When using this product

- use only as directed
- do not wear if you are allergic to any material in this product or chili peppers
- do not apply to wounds, damaged or irritated skin
- do not get into eyes or on mucous membranes
- do not use with heating pad or other external analgesic products
- a slight burning sensation may occur upon application in some cases
- if severe burning sensation occurs, discontinue use immediately
- do not use 1 hour prior to bathing or within 30 minutes after bathing

Stop use and ask a doctor if

- conditions worsen
- severe skin irritation occurs
- pain persists for more than 7 days
- symptoms clear up and occur again within a few days

If pregnant or breast-feeding

Ask a health professional before use.

Keep out of reach children

If swallowed, get medical help or contact a Poison Control Center right away.

Directions

- clean and dry affected area
- remove sleeve from packaging and place on elbow
- maximum use of 10 hours per day

Product care instructions

- wash separately from other clothes
- do not store in direct sunlight
- protect product from excessive moisture when not in use

Inactive ingredient

acrylate copolymer